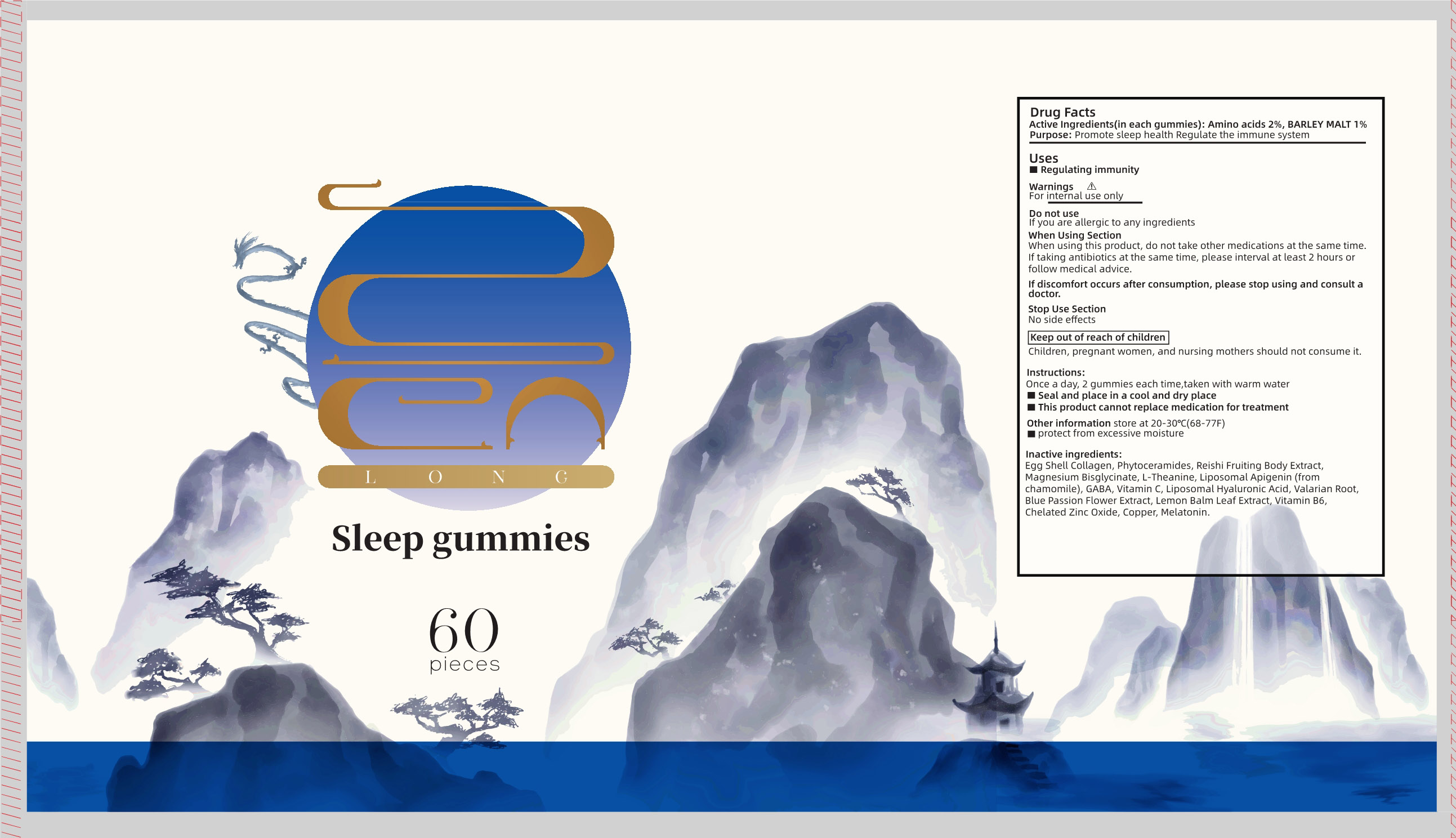 DRUG LABEL: Sleep gummies
NDC: 83739-004 | Form: CHEWABLE GEL
Manufacturer: XIAN CHIANG COMPANY LIMITED
Category: otc | Type: HUMAN OTC DRUG LABEL
Date: 20250216

ACTIVE INGREDIENTS: BARLEY MALT 1 g/100 1; AMINO ACIDS 2 g/100 1
INACTIVE INGREDIENTS: MELISSA OFFICINALIS LEAF; VALERIAN; ASCORBIC ACID; CERAMIDE 2; REISHI; MAGNESIUM GLYCINATE; COPPER; ZINC OXIDE; PENICILLOYL POLYLYSINE; THEANINE; PASSIFLORA CAERULEA FRUIT; MELATONIN; PYRIDOXINE; APIGENIN; .GAMMA.-AMINOBUTYRIC ACID; HYALURONIC ACID

83739-004

Active Ingredient

Amino acids 2%, BARLEY MALT 1%

Purpose

Promote sleep health Regulate the immune system

Uses

Regulating immunity

Warnings

For internal use only

Do not use

If you are allergic to any ingredients

When Using Section

When using this product , do not take other medications at the same timeIf taking antibiotics at the same time , please interval at least 2 hours ofollow medical advice

If discomfort occurs after consumption , please stop using and consult a doctor

Stop Use Section

No side effects

Keep out of reach of childre

Children , pregnant women , and nursing mothers should not consume it

Instructions

Once a day , 2 gummies each time , taken with warm water

Seal and place in a cool and dry place

This product cannot replace medication for treatment

Other information

Other information store at 20-30°C (68-77F)

protect from excessive

inactive ingredients

Egg Shell Collagen , Phytoceramides , Reishi Fruiting Body Extract ,Magnesium Bisglycinate , L-Theanine , Liposomal Apigenin (from chamomile) , GABA , Vitamin C , Liposomal Hyaluronic Acid , Valarian Root, Blue Passion Flower Extract , Lemon Balm Leaf Extract , Vitamin B6, Chelated Zinc Oxide , Copper , Melatonin.